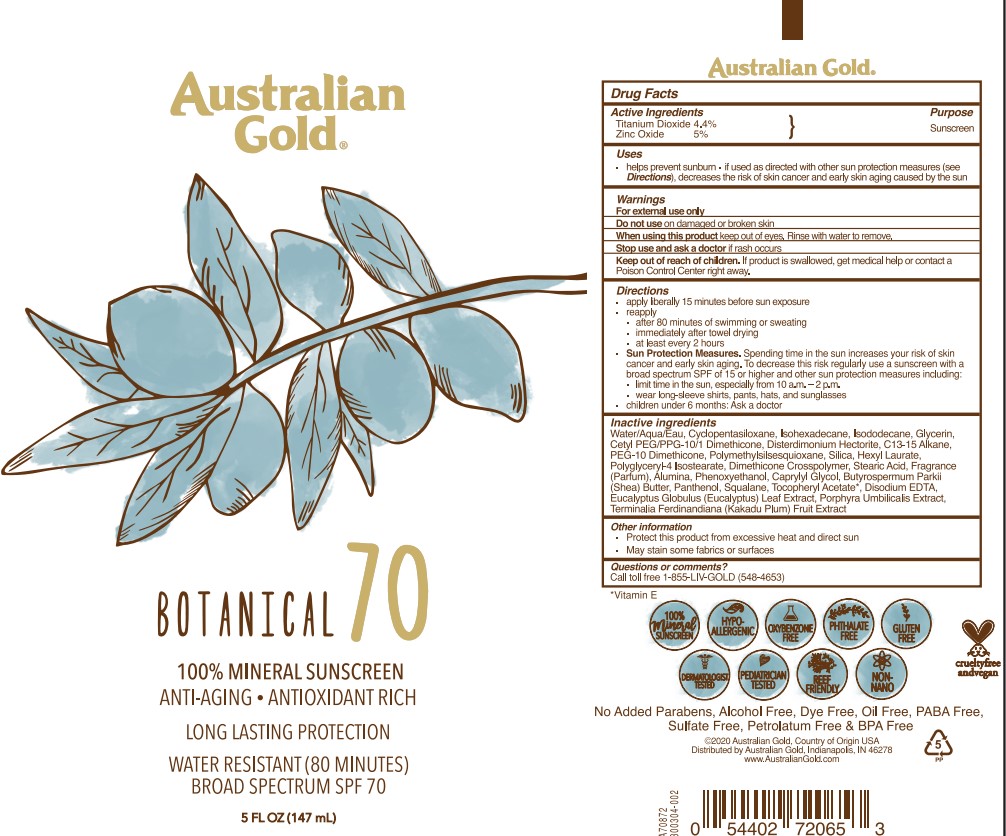 DRUG LABEL: Australian Gold
NDC: 58443-0508 | Form: LOTION
Manufacturer: Prime Enterprises Inc.
Category: otc | Type: HUMAN OTC DRUG LABEL
Date: 20220114

ACTIVE INGREDIENTS: TITANIUM DIOXIDE 44.26 mg/1 mL; ZINC OXIDE 50.3 mg/1 mL
INACTIVE INGREDIENTS: ALUMINUM OXIDE; CETYL PEG/PPG-10/1 DIMETHICONE (HLB 2); DIMETHICONE CROSSPOLYMER (450000 MPA.S AT 12% IN CYCLOPENTASILOXANE); C13-15 ALKANE; PHENOXYETHANOL; ISOHEXADECANE; ISODODECANE; POLYGLYCERYL-4 ISOSTEARATE; CYCLOMETHICONE 5; WATER; SHEA BUTTER; CAPRYLYL GLYCOL; PANTHENOL; SILICON DIOXIDE; SQUALANE; .ALPHA.-TOCOPHEROL ACETATE; KAKADU PLUM; STEARIC ACID; EUCALYPTUS GLOBULUS LEAF; EDETATE DISODIUM; DISTEARDIMONIUM HECTORITE; GLYCERIN; POLYMETHYLSILSESQUIOXANE (4.5 MICRONS); PORPHYRA UMBILICALIS; HEXYL LAURATE; PEG-10 DIMETHICONE (600 CST)

Australian Gold Botanical Sunscreen 70 Mineral Lotion

Active Ingredients

Titanium Dioxide 4.4%

Zinc Oxide 5%

Purpose

Sunscreen

Uses

- helps prevent sunburn
- if used as directed with other sun protection measures (see Directions), decreases the risk of skin cancer and early skin aging caused by the sun

Warnings

For external use only

Do not use on damaged or broken skin

When using this product keep out of eyes. Rinse with water to remove

Stop use and ask a doctor if rash occurs

Keep out of reach of children. If product is swallowed, get medical help or contact a Poison Control Center right away.

Directions

- apply liberally 15 minutes before sun exposure
- reapply
- after 80 minutes of swimming or sweating
- immediately after towel drying
- at least every 2 hours
- Sun Protection Measures. Spending time in the sun increases your risk of skin cancer and early skin aging. To decrease this risk, regularly use a sunscreen with broad spectrum SPF of 15 or higher and other sun protection measures including:
- limit time in the sun, especially from 10 a.m. – 2 p.m.
- wear long-sleeve shirts, pants, hats, and sunglasses
- children under 6 months: Ask a doctor

Inactive Ingredients

Alumina, Butyrospermum Parkii (Shea) Butter, C13-15 Alkane, Caprylyl Glycol, Cetyl PEG/PPG-10/1 Dimethicone, Cyclopentasiloxane, Dimethicone Crosspolymer, Disodium EDTA, Disterdimonium Hectorite, Eucalyptus Globulus (Eucalyptus) Leaf Extract, Fragrance (Parfum), Glycerin, Hexyl Laurate, Isododecane, Isohexadecane, Panthenol, PEG-10 Dimethicone, Phenoxyethanol, Polyglyceryl-4 Isostearate, Polymethylsilsesquioxane, Porphyra Umbilicalis Extract, Silica, Squalane, Stearic Acid, Terminalia Ferdinandiana (Kakadu Plum) Fruit Extract, Tocopheryl Acetate, Water/Aqua/Eau

Other information

- Protect this product from excessive heat and direct sun
- May stain some fabrics or surfaces

Questions or comments?

Call toll free 1-855-LIV-GOLD (548-4653)